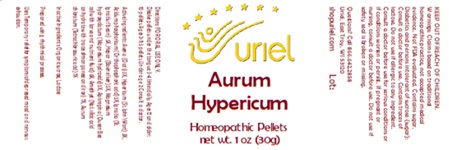 DRUG LABEL: Aurum Hypericum
NDC: 48951-1281 | Form: PELLET
Manufacturer: Uriel Pharmacy Inc
Category: homeopathic | Type: HUMAN OTC DRUG LABEL
Date: 20250110

ACTIVE INGREDIENTS: OAT 3 [hp_X]/1 1; HYPERICUM PERFORATUM 3 [hp_X]/1 1; PHOSPHORIC ACID 5 [hp_X]/1 1; STRYCHNOS IGNATII SEED 5 [hp_X]/1 1; MAMMAL LIVER 5 [hp_X]/1 1; MAGNESIUM 5 [hp_X]/1 1; APIS MELLIFERA 6 [hp_X]/1 1; SILICON DIOXIDE 7 [hp_X]/1 1; GOLD TRICHLORIDE 7 [hp_X]/1 1
INACTIVE INGREDIENTS: SUCROSE; LACTOSE, UNSPECIFIED FORM

Aurum Hypericum Pellets

INDICATIONS AND USAGE

Directions: FOR ORAL USE ONLY.

DOSAGE AND ADMINISTRATION

Dissolve pellets under the tongue 3-4
times daily. Ages 12 and older: 10 pellets. Ages 2-11: 5 pellets. Under age 2: Consult a doctor.

ACTIVE INGREDIENT

Active Ingredients: Avena (Oats) 3X, Hypericum (St. John’s Wort) 3X, Acidum phosphoricum (Orthophosphoric acid) 5X, Ignatia (St. Ignatius’ bean) 5X, Hepar (Bovine liver) 5X, Magnesium hydroxydatum (Magnesium hydroxide) 5X, Apis regina (Queen Bee cell with larva and nutrient fluid) 6X, Amethyst (Nat. silicic acid anhydrate with traces of manganese and iron) 7X, Aurum chloratum (Tetrachloroauric acid) 7X

Inactive Ingredients: Organic sucrose, Lactose

Prepared using rhythmical processes.

PURPOSE

Uses: Temporary relief for symptoms of depressed mood and nervous exhaustion.

KEEP OUT OF REACH OF CHILDREN.

WARNINGS

Warnings: Claims based on traditional homeopathic practice, not accepted medical evidence. Not FDA evaluated. Contains sugar. Diabetics and persons intolerant of sucrose (sugar): Consult a doctor before use. Do not use if allergic to any ingredient. Contains traces of lactose. Consult a doctor before use for serious conditions or if conditions worsen or persist. If pregnant or nursing, consult a doctor before use. Do not use if safety seal is broken or missing.

Questions? Call 866.642.2858
Uriel, East Troy, WI 53120
shopuriel.com